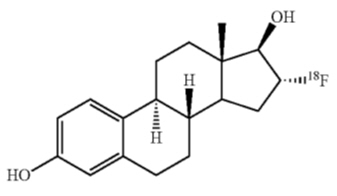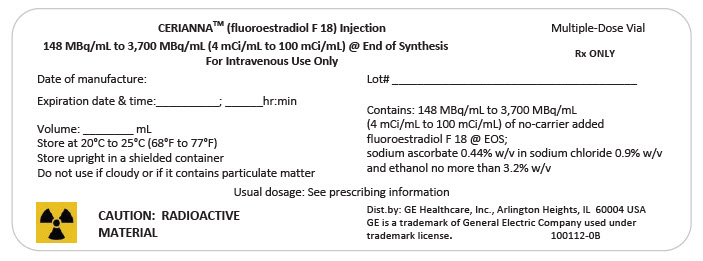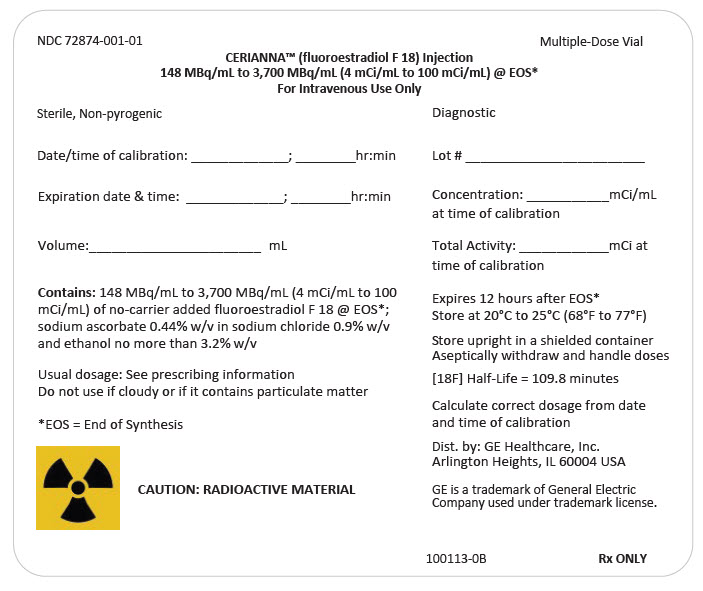 DRUG LABEL: CERIANNA
NDC: 72874-001 | Form: INJECTION
Manufacturer: GE Healthcare Inc.
Category: prescription | Type: HUMAN PRESCRIPTION DRUG LABEL
Date: 20251231

ACTIVE INGREDIENTS: FLUOROESTRADIOL F-18 100 mCi/1 mL
INACTIVE INGREDIENTS: SODIUM ASCORBATE; SODIUM CHLORIDE; ALCOHOL

HIGHLIGHTS OF PRESCRIBING INFORMATION

These highlights do not include all the information needed to use CERIANNA™ safely and effectively. See full prescribing information for CERIANNA.
CERIANNA™ (fluoroestradiol F 18) Injection, for intravenous use
Initial U.S. Approval: 2020

1 INDICATIONS AND USAGE

CERIANNA is a radioactive diagnostic agent indicated for use with positron emission tomography (PET) imaging for the detection of estrogen receptor (ER)-positive lesions as an adjunct to biopsy in patients with recurrent or metastatic breast cancer. (1)

Limitations of Use

Tissue biopsy should be used to confirm recurrence of breast cancer and to verify ER status by pathology. CERIANNA is not useful for imaging other receptors, such as human epidermal growth factor receptor 2 (HER2) and the progesterone receptor (PR). (1, 5.1)

2 DOSAGE AND ADMINISTRATION

- Recommended dose is 222 MBq (6 mCi), with a range of 111 MBq to 222 MBq (3 mCi to 6 mCi), administered as an intravenous injection over 1 to 2 minutes. (2.2)
- Recommended imaging start time is 80 minutes (range 20 minutes to 80 minutes) after drug administration. (2.4)
- See full prescribing information for additional preparation, administration, imaging, and radiation dosimetry information. (2)

3 DOSAGE FORMS AND STRENGTHS

Injection: 148 MBq/mL to 3,700 MBq/mL (4 mCi/mL to 100 mCi/mL) of fluoroestradiol F 18 in a multiple-dose vial. (3)

4 CONTRAINDICATIONS

- None. (4)

5 WARNINGS AND PRECAUTIONS

- Risk of Misdiagnosis. Do not use CERIANNA in lieu of biopsy when biopsy is indicated in patients with recurrent or metastatic breast cancer. Pathology or clinical characteristics that suggest a patient may benefit from systemic hormone therapy should take precedence over a discordant negative CERIANNA scan. (5.1)
- Radiation Risks. Ensure safe drug handling and patient preparation procedures to protect patients and health care providers from unintentional radiation exposure. (2.1, 2.3, 5.2)

6 ADVERSE REACTIONS

Reported adverse reactions include: injection-site pain and dysgeusia (6)

To report SUSPECTED ADVERSE REACTIONS, contact GE HealthCare at 1-800-654-0118 or FDA at 1-800-FDA-1088 or www.fda.gov/medwatch.

7 DRUG INTERACTIONS

- Before administering CERIANNA, discontinue drugs that bind to the ER, such as SERMs and SERDs, for at least 5 biological half-lives (e.g., elacestrant for 11 days, tamoxifen for 8 weeks, and fulvestrant for 28 weeks). (2.3, 7)

8 USE IN SPECIFIC POPULATIONS

- Lactation: Interrupt breastfeeding. Advise a lactating woman to avoid breastfeeding for 4 hours after CERIANNA administration. (8.2)

FULL PRESCRIBING INFORMATION

1 INDICATIONS AND USAGE

CERIANNA is indicated for use with positron emission tomography (PET) imaging for the detection of estrogen receptor (ER)-positive lesions as an adjunct to biopsy in patients with recurrent or metastatic breast cancer.

Limitations of Use

Tissue biopsy should be used to confirm recurrence of breast cancer and to verify ER status by pathology. CERIANNA is not useful for imaging other receptors, such as human epidermal growth factor receptor 2 (HER2) and the progesterone receptor (PR).

2 DOSAGE AND ADMINISTRATION

2.1 Radiation Safety - Drug Handling

CERIANNA is a radioactive drug. Only authorized persons qualified by training and experience should receive, use, and administer CERIANNA. Handle CERIANNA with appropriate safety measures to minimize radiation exposure during administration [see Warnings and Precautions (5.2)]. Use waterproof gloves and effective radiation shielding, including syringe shields, when preparing and handling CERIANNA.

2.2 Recommended Dosage and Administration Instructions

Recommended Dosage

The recommended amount of radioactivity to be administered for PET imaging is 222 MBq (6 mCi), with a range of 111 MBq to 222 MBq (3 mCi to 6 mCi), administered as a single intravenous injection of 10 mL or less over 1 to 2 minutes.

Preparation and Administration

- For patient preparation instructions, see Dosage and Administration 2.3.
- Use aseptic technique and radiation shielding when withdrawing and administering CERIANNA.
- Visually inspect the radiopharmaceutical solution. Do not use if it contains particulate matter or if it is cloudy or discolored (CERIANNA is a clear, colorless solution).
- CERIANNA may be diluted with 0.9% Sodium Chloride Injection, USP.
- Assay the dose in a suitable dose calibrator prior to administration.

Post-Administration Instructions

- Follow the CERIANNA injection with an intravenous flush of 0.9% Sodium Chloride injection, USP.
- Dispose of any unused CERIANNA in compliance with applicable regulations.

2.3 Patient Preparation

Assessment for Drug Interactions

Before administering CERIANNA, discontinue drugs that bind to ER (e.g., selective estrogen receptor modulators (SERMs) and selective estrogen receptor down-regulators (SERDs)) [see Drug Interactions (7)].

Patient Hydration and Voiding

Instruct patients to drink water to ensure adequate hydration prior to administration of CERIANNA and to continue drinking and voiding frequently during the first hours following administration to reduce radiation exposure.

Pregnancy Status

Assessment of pregnancy status is recommended in females of reproductive potential before administering CERIANNA.

2.4 Image Acquisition

Position the patient supine with arms above the head, if possible. The recommended start time for image acquisition is 80 minutes after the intravenous administration of CERIANNA. Scan duration adapted from the range of 20 minutes to 30 minutes and imaging start times adapted within the range of 20 minutes to 80 minutes may be customized according to the equipment used and patient and tumor characteristics for optimal image quality.

2.5 Image Interpretation

Uptake of fluoroestradiol F 18 depends on ER density and function in tumors and physiologic tissue, including in liver, ovary, and uterus. Detection of ER-positive tumors should be based on comparison with tissue background outside of organs with high physiologic uptake and regions with high activity due to hepatobiliary and urinary excretion.

2.6 Radiation Dosimetry

Radiation absorbed dose estimates are shown in Table 1 for organs and tissues of adults from intravenous administration of CERIANNA. The radiation effective dose resulting from administration of 222 MBq (6 mCi) of CERIANNA to an adult weighing 70 kg is estimated to be 4.9 mSv. Critical organs include the liver, gallbladder, and uterus. When PET/CT is performed, exposure to radiation will increase by an amount dependent on the settings used for the CT acquisition.

Table 1. Estimated Radiation Absorbed Doses in Various Organs/Tissues in Adults Who Received FLUOROESTRADIOL F 18
Organ | Mean Absorbed Dose Per Unit of Activity Administered (mGy/MBq)
Adrenals | 0.023
Brain | 0.01
Breasts | 0.009
Gallbladder | 0.102
Lower large intestine | 0.012
Small intestine | 0.027
Stomach | 0.014
Upper large intestine | 0.03
Heart wall | 0.026
Kidney | 0.035
Liver | 0.126
Lungs | 0.017
Muscle | 0.021
Ovaries | 0.018
Pancreas | 0.023
Red Marrow | 0.013
Bone surface | 0.014
Skin | 0.005
Spleen | 0.015
Testes | 0.012
Thymus | 0.014
Thyroid | 0.012
Urinary bladder | 0.05
Uterus | 0.039
Lens | 0.009
Effective dose = 0.022 mSv/MBq

3 DOSAGE FORMS AND STRENGTHS

Injection: clear, colorless solution in a multiple-dose vial containing 148 MBq/mL to 3,700 MBq/mL (4 mCi/mL to 100 mCi/mL) of fluoroestradiol F 18 at end of synthesis.

4 CONTRAINDICATIONS

None.

5 WARNINGS AND PRECAUTIONS

5.1 Risk of Misdiagnosis

Inadequate Tumor Characterization and Other ER-Positive Pathology

Breast cancer may be heterogeneous within patients and across time. CERIANNA images ER and is not useful for imaging other receptors such as HER2 and PR. The uptake of fluoroestradiol F 18 is not specific for breast cancer and may occur in a variety of ER-positive tumors that arise outside of the breast, including from the uterus and ovaries. Do not use CERIANNA in lieu of biopsy when biopsy is indicated in patients with recurrent or metastatic breast cancer.

False Negative CERIANNA Scan

A negative CERIANNA scan does not rule out ER-positive breast cancer [see Clinical Studies (14)]. Pathology or clinical characteristics that suggest a patient may benefit from systemic hormone therapy should take precedence over a discordant negative CERIANNA scan.

5.2 Radiation Risks

Diagnostic radiopharmaceuticals, including CERIANNA, expose patients to radiation [see Dosage and Administration (2.6)]. Radiation exposure is associated with a dose-dependent increased risk of cancer. Ensure safe drug handling and patient preparation procedures to protect patients and health care providers from unintentional radiation exposure [see Dosage and Administration (2.1) and (2.3)].

6 ADVERSE REACTIONS

6.1 Clinical Trials Experience

Because clinical trials are conducted under widely varying conditions, adverse reaction rates observed in the clinical trials of a drug cannot be directly compared to rates in the clinical trials of another drug and may not reflect the rates observed in practice.

The safety of CERIANNA was evaluated from published clinical studies of 1,207 patients with breast cancer receiving at least one fluoroestradiol F 18 administration. The following adverse reactions occurred at a rate < 1%:

- General disorders: injection-site pain
- Neurological and gastrointestinal disorders: dysgeusia

7 DRUG INTERACTIONS

Drugs that bind to the estrogen receptor (ER) may compete with the binding of fluoroestradiol F 18 and may reduce the detection of ER-positive lesions with CERIANNA.

Before administering CERIANNA, discontinue drugs that bind to the ER, such as SERMs and SERDs, for at least 5 biological half-lives (e.g., elacestrant for 11 days, tamoxifen for 8 weeks, and fulvestrant for 28 weeks) [see Dosage and Administration (2.3)].

8 USE IN SPECIFIC POPULATIONS

8.1 Pregnancy

Risk Summary

All radiopharmaceuticals, including CERIANNA, have the potential to cause fetal harm depending on the fetal stage of development and the magnitude of radiation dose. Advise a pregnant woman of the potential risks of fetal exposure to radiation from administration of CERIANNA.

There are no available data on CERIANNA use in pregnant women. No animal reproduction studies using fluoroestradiol F 18 have been conducted to evaluate its effect on female reproduction and embryo-fetal development.

The estimated background risk of major birth defects and miscarriage for the indicated populations is unknown. All pregnancies have a background risk of birth defects, loss, or other adverse outcomes. In the U.S. general population, the estimated background risk of major birth defects and miscarriage in clinically recognized pregnancies is 2% to 4% and 15% to 20%, respectively.

8.2 Lactation

Risk Summary

There are no data on the presence of fluoroestradiol F 18 in human milk, or its effects on the breastfed infant or milk production. Lactation studies have not been conducted in animals. Advise a lactating woman to avoid breastfeeding for 4 hours after CERIANNA administration in order to minimize radiation exposure to a breastfed infant.

8.4 Pediatric Use

The safety and effectiveness of CERIANNA in pediatric patients have not been established.

8.5 Geriatric Use

Clinical studies of fluoroestradiol F 18 injection did not reveal any difference in pharmacokinetics or biodistribution in patients aged 65 and over.

11 DESCRIPTION

11.1 Chemical Characteristics

CERIANNA contains fluoroestradiol fluorine 18 (F 18), a synthetic estrogen analog. Chemically, fluoroestradiol F 18 is [18F]16α-fluoro-3,17β-diol-estratriene-1,3,5(10). The molecular weight is 289.37, and the structural formula is:

CERIANNA is a sterile, clear, colorless solution for intravenous injection, with an osmolarity of 340 mOsm. Its pH ranges between 5.5 to 8.0. The composition of the final product in 40 mL solution is fluoroestradiol no more than 5 mcg, fluoroestradiol F 18 148 MBq/mL to 3,700 MBq/mL (4 mCi/mL to 100 mCi/mL), sodium ascorbate 0.44% w/v in sodium chloride 0.9% w/v, and ethanol no more than 3.2% w/v.

11.2 Physical Characteristics

CERIANNA is radiolabeled with F 18, a cyclotron produced radionuclide that decays by positron emission to stable oxygen 18 with a half-life of 109.8 minutes. The principal photons useful for diagnostic imaging are the coincident pair of 511 keV gamma photons, resulting from the interaction of the emitted positron with an electron (Table 2).

Table 2. Principal Radiation Produced From Decay of Fluorine 18 Radiation
Radiation | Energy Level (keV) | % Abundance
Positron | 249.8 | 96.9
Gamma | 511 | 193.5

11.3 External Radiation

The point source air-kerma coefficient for F 18 is 3.75 × 10^-17 Gy m^2 / (Bq s). The first half-value thickness of lead (Pb) for F 18 gamma rays is approximately 6 mm. The relative reduction of radiation emitted by F 18 that results from various thicknesses of lead shielding is shown in Table 3. The use of 8 cm Pb decreases the radiation transmission (i.e., exposure) by a factor of about 10,000.

Table 3. Radiation Attenuation of 511 keV Gamma Rays by Lead Shielding
Shield Thickness cm of Lead (Pb) | Coefficient of Attenuation
0.6 | 0.5
2 | 0.1
4 | 0.01
6 | 0.001
8 | 0.0001

12 CLINICAL PHARMACOLOGY

12.1 Mechanism of Action

Fluoroestradiol F 18 binds ER. The following binding affinity: Kd = 0.13 ± 0.02 nM, Bmax = 1901 ± 89 fmol/mg, and IC50 = 0.085 nM, was determined in an ER-positive human breast cancer cell line (MCF-7).

12.2 Pharmacodynamics

The relationship between fluoroestradiol F18 plasma concentrations and image interpretation has not been studied. Fluoroestradiol F18 uptake measured by PET in human tumors is directly proportional to tumor ER expression measured by in vitro assays.

12.3 Pharmacokinetics

Distribution

After intravenous injection, 95% of fluoroestradiol F 18 is bound to plasma proteins. Fluoroestradiol F 18 distributes primarily to hepatobiliary system, and also to small and large intestines, heart wall, blood, kidney, uterus and bladder.

Metabolism

Fluoroestradiol F 18 is metabolized in the liver. At 20 minutes after injection, approximately 20% of circulating radioactivity in the plasma is in the form of non-metabolized fluoroestradiol F 18. At 2 hours after injection, circulating fluoroestradiol F 18 levels are less than 5% of peak concentration.

Excretion

Elimination is by biliary and urinary excretion.

13 NONCLINICAL TOXICOLOGY

13.1 Carcinogenesis, Mutagenesis, Impairment of Fertility

Carcinogenesis

No long-term studies in animals were performed to evaluate the carcinogenic potential of CERIANNA.

Mutagenesis

Fluoroestradiol was evaluated by in vitro bacterial reverse mutation assay (Ames test) and in vitro L5178Y/TK+/- mouse lymphoma mutagenesis assay. Fluoroestradiol was negative for genotoxicity by Ames test at up to 1.25 µg per plate for 5 tester strains (Salmonella typhimurium tester strains TA98, TA100, TA1535 and TA1537 and Escherichia Coli tester strain WP2 uvrA) in the presence or absence of S9 metabolic activation. Fluoroestradiol was negative for genotoxicity by L5178Y/TK+/- mouse lymphoma mutagenesis assay at up to 8 ng/mL in the absence or presence of S9 metabolic activation.

Potential in vivo genotoxicity of fluoroestradiol was evaluated in a rat micronucleus assay. In this assay, fluoroestradiol did not increase the number of micronucleated polychromatic erythrocytes (MN-PCEs) at 51 µg/kg/day, when given for 14 consecutive days. However, CERIANNA has the potential to be mutagenic because of the F 18 radioisotope.

Impairment of Fertility

No studies in animals have been performed to evaluate potential impairment of fertility in males or females.

14 CLINICAL STUDIES

The effectiveness of CERIANNA for detecting ER-positive non-primary breast cancer lesions was evaluated based on published study reports of fluoroestradiol F 18. Study 1 (NCT01986569) enrolled 90 women (median age 55 years, 39% premenopausal) with histologically confirmed invasive breast cancer. The patients had first known or suspected recurrence of treated breast cancer or stage IV metastatic breast cancer. Recent biopsy of lesions outside of bone and areas with high physiologic fluoroestradiol F 18 uptake was also required [see Dosage and Administration (2.5)]. Patients concurrently using estrogen receptor modulators or fulvestrant discontinued them 60 days prior to fluoroestradiol F 18 administration. Concurrent use of aromatase inhibitors was permitted. Three image readers were blinded to all clinical information, except for the location of the largest biopsied lesion, for which pathologists independently provided an Allred score (0 to 8). The image readers scored the intensity of FES uptake on a three-point scale relative to normal biodistribution as either "decreased," "equivocal," or "increased" (1 to 3).

Image reader performance for distinguishing between ER-positive and ER-negative fluoroestradiol F 18 uptake was compared to biopsy in 85 patients. Of the 47 patients with positive biopsy (Allred score ≥ 3), 36 were positive on imaging (majority reader score = 3). Ten of 11 patients with false negative imaging had Allred scores between 3 and 6 [see Warnings and Precautions (5.1)]. Of the 38 patients with negative biopsy, all 38 were negative on imaging.

Study 2 (NCT00602043) in 13 patients showed similar results.

16 HOW SUPPLIED/STORAGE AND HANDLING

16.1 How Supplied

CERIANNA is supplied in a 50 mL multiple-dose glass vial (NDC 72874-001-01) containing a clear, colorless injection solution at a strength of 148 MBq/mL to 3,700 MBq/mL (4 mCi/mL to 100 mCi/mL) fluoroestradiol F 18 at the end of synthesis. Each vial contains multiple doses and is enclosed in a shield container to minimize external radiation exposure.

16.2 Storage and Handling

Storage

Store CERIANNA at controlled room temperature (USP) 20°C to 25°C (68°F to 77°F). Store CERIANNA upright in the original container with radiation shielding. The expiration date and time are provided on the container label. Use CERIANNA within 12 hours from the time of the end of synthesis.

Handling

This preparation is approved for use by persons under license by the Nuclear Regulatory Commission or the relevant regulatory authority of an Agreement State.

17 PATIENT COUNSELING INFORMATION

Radiation Risks

Advise patients of the radiation risks of CERIANNA [see Warnings and Precautions (5.2)]. Instruct patients to drink water to ensure adequate hydration prior to administration of CERIANNA and to continue drinking and voiding frequently during the first hours following administration to reduce radiation exposure [see Dosage and Administration (2.3)].

Pregnancy

Advise a pregnant woman of the potential risks of fetal exposure to radiation doses with CERIANNA [see Use in Specific Populations (8.1)].

Lactation

Advise a lactating woman to avoid breastfeeding for 4 hours after CERIANNA administration in order to minimize radiation exposure to a breastfed infant [see Use in Specific Populations (8.2)].

© 2025 GE HealthCare
Distributed by GE Healthcare Inc., Arlington Heights, IL 60004 U.S.A.
GE is a trademark of General Electric Company used under trademark license.

PRINCIPAL DISPLAY PANEL - 50 mL Vial Label

CERIANNA™ (fluoroestradiol F 18) Injection
148 MBq/mL to 3,700 MBq/mL (4 mCi/mL to 100 mCi/mL) @ End of Synthesis
For Intravenous Use Only

Multiple-Dose Vial
Rx ONLY

Date of manufacture:

Expiration date & time:__________; ______hr:min

Lot# _______________________________________

Volume: ________ mL
Store at 20°C to 25°C (68°F to 77°F)
Store upright in a shielded container
Do not use if cloudy or if it contains particulate matter

Contains: 148 MBq/mL to 3,700 MBq/mL
(4 mCi/mL to 100 mCi/mL) of no-carrier added
fluoroestradiol F 18 @ EOS;
sodium ascorbate 0.44% w/v in sodium chloride 0.9% w/v
and ethanol no more than 3.2% w/v

Usual dosage: See prescribing information

CAUTION: RADIOACTIVE
MATERIAL

Dist.by: GE Healthcare, Inc., Arlington Heights, IL 60004 USA
GE is a trademark of General Electric Company used under
trademark license.

100112-0B

PRINCIPAL DISPLAY PANEL - 50 mL Vial Shield Label

NDC 72874-001-01

Multiple-Dose Vial

CERIANNA™ (fluoroestradiol F 18) Injection
148 MBq/mL to 3,700 MBq/mL (4 mCi/mL to 100 mCi/mL) @ EOS*
For Intravenous Use Only

Sterile, Non-pyrogenic
Diagnostic

Date/time of calibration: _____________; ________hr:min

Expiration date & time: _____________; ________hr:min

Volume: _______________________ mL

Lot # ________________________

Concentration: ___________mCi/mL
at time of calibration

Total Activity: ____________mCi at
time of calibration

Contains: 148 MBq/mL to 3,700 MBq/mL (4 mCi/mL to 100
mCi/mL) of no-carrier added fluoroestradiol F 18 @ EOS*;
sodium ascorbate 0.44% w/v in sodium chloride 0.9% w/v
and ethanol no more than 3.2% w/v

Usual dosage: See prescribing information
Do not use if cloudy or if it contains particulate matter

*EOS = End of Synthesis

CAUTION: RADIOACTIVE MATERIAL

Expires 12 hours after EOS*
Store at 20°C to 25°C (68°F to 77°F)

Store upright in a shielded container
Aseptically withdraw and handle doses

[18F] Half-Life = 109.8 minutes

Calculate correct dosage from date
and time of calibration

Dist. by: GE Healthcare, Inc.
Arlington Heights, IL 60004 USA

GE is a trademark of General Electric
Company used under trademark license.

100113-0B

Rx ONLY